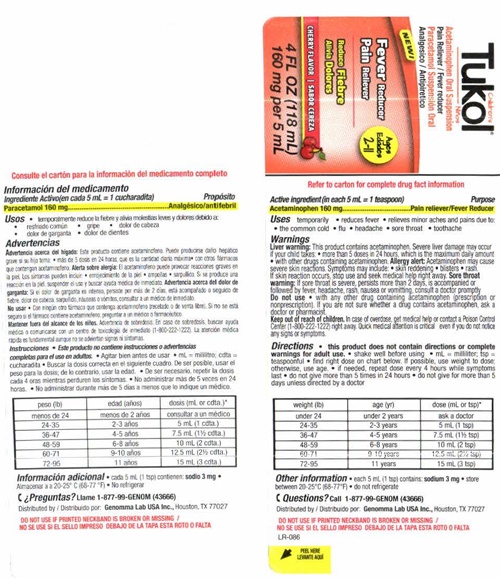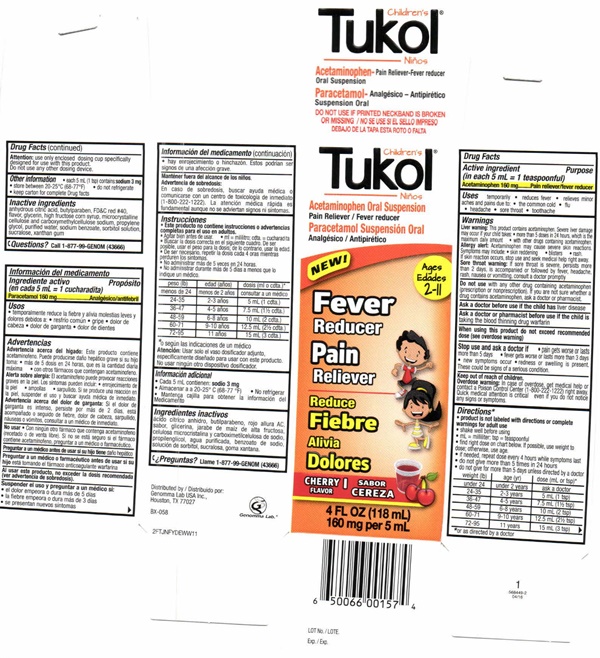 DRUG LABEL: Childrens Tukol Acetaminophen Fever Reducer Pain Reducer
NDC: 50066-525 | Form: LIQUID
Manufacturer: Genomma Lab USA, Inc.
Category: otc | Type: HUMAN OTC DRUG LABEL
Date: 20170415

ACTIVE INGREDIENTS: ACETAMINOPHEN 160 mg/5 mL
INACTIVE INGREDIENTS: ANHYDROUS CITRIC ACID; BUTYLPARABEN; FD&C RED NO. 40; GLYCERIN; HIGH FRUCTOSE CORN SYRUP; MICROCRYSTALLINE CELLULOSE; CARBOXYMETHYLCELLULOSE SODIUM; PROPYLENE GLYCOL; WATER; SODIUM BENZOATE; SORBITOL; SUCRALOSE; XANTHAN GUM

Children's Tukol® Fever Pain 525

Drug Facts Active ingredient (in each 5 mL = 1 teaspoonful)

Acetaminophen 160 mg

Purpose

Pain reliever/fever reducer

Uses

temporarily

- reduces fever
- relieves minor aches and pains due to:
- the common cold
- flu
- headache
- sore throat
- toothache

Warnings

Liver warning: This product cantains acetaminophen. Severe liver damage may occur if your child takes

- more than 5 doses in 24 hours which is the maxium daily amount
- with other drugs containing acetaminophen

Allergy alert: Acetaminophen may cause severe skin reactions. Symptoms may include:

- skin reddening
- blisters
- rash

If skin reaction occurs, stop use and seek medical help right away.

Sore throat warning: if sore throat is severe, persists more than 2 days, is accompanied or followed by fever, headache, rash, nausea or vomitting, consult a doctor promptly.

Do not use

- with any other drug containing acetaminophen (prescription or non prescription). If you are not sure whether a drug containd acetaminophen, ask a doctor or pharmacist

Ask a doctor before use if the child has

liver disease

Ask a doctor or pharmacist before use if the child is

taking the blood thinning drug warfarin.

When using this product

do not exceed recommended dose (see overdose warning)

Stop use and ask a doctor if

- pain gets worse or lasts more than 5 days
- fever gets worse or lasts more tha 3 days
- new symptoms occur
- redness or swelling is present

These could be signs of a serious condition

Keep out of reach of children.

Overdose warning:

In case of overdose, get medical help or contact a Poison Control Center (1-800-222-1222) right away.
Quick medical attention is critical even if you do not notice any signs or symptoms.

Directions *

- product is not labeled with directions or complete warning for adult use
- Shake well before using
- 1mL = milliliter; tsp = teaspoonful
- find the right dose on chart below. If posssible, use weight to dose: otherwise use age.
- if needed, repeat dose every 4 hours while symptons last
- do not give more than 5 times in 24 hours
- do not give for more than 5 days unless directed by a doctor

weight (lb) age dose (mL or tsp)

under 24 under 2 years ask a doctor

24 - 35 2 - 3 years 5 mL (1 tsp)

36- 47 4 - 5 years 7.5 mL (1 1/2 tsp)

48 - 59 6 - 8 years 10 mL (10 mL (2 tsp)

60- 71 9 - 10 years 12.5 mg (2 1/2 tsp)

72 95 11 years 15 mL (3 tsp)

use only enclosed dosing cup specfically designed for use with this product

Attention:

use only enclosed dosing cup specfically designed for use with this product

Other information

- each 5 mL (1 tsp) contains: sodium 3 mg
- store between 20-25°C (68-77°F)
- do not refrigerate
- keep carton for complete Drug facts

Inactive ingredients

anhydrous citric acid, butylparaben, FD&C red # 40, flavor, glycerin, high fructose corn syrup, microcrystalline cellulose and carboxymethylcellulose sodium, propylene glycol, purified water, sodium benzoate, sorbitol solution, sucralose, xanthan gum

Questions?

Call 1-877-99-GENOM (43666)

Children's Tukol® Fever Pain product label

Children's Tukol®

Acetaminophen - Pain Reliever-Fever Reducer Oral Suspension

DO NOT USE IF PRINTED NECKBAND IS BROKEN OR MISSION

NEW

Ages 2 - 11

Fever Reducer

Pain Reducer

CHERRY FLAVOR

4 FL OZ (118 mL)
160 mg per 5 mL

Distributer by
Genomma Lab USA Inc.,
Houston, TX 77027

BX--058

LOT No.

Exp.